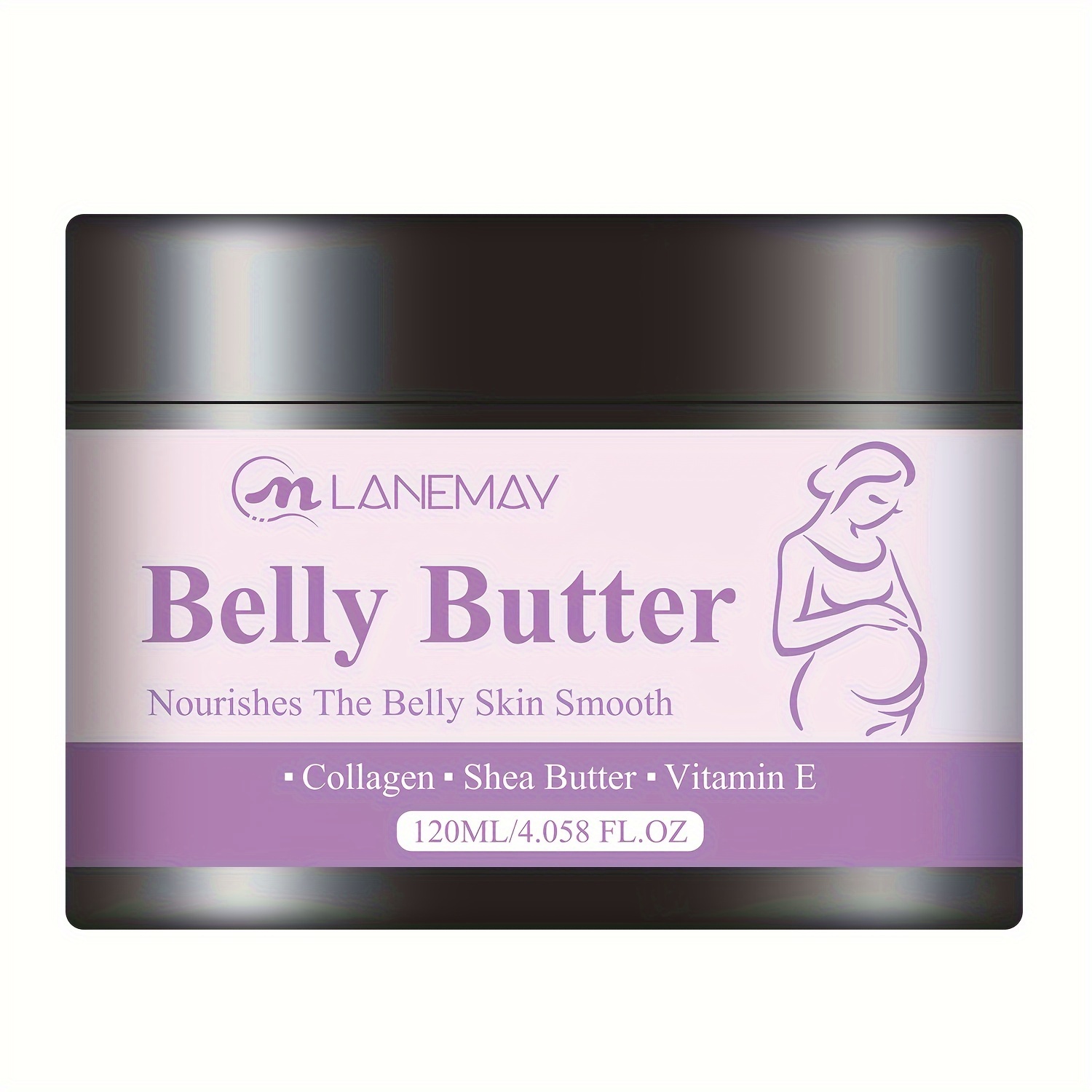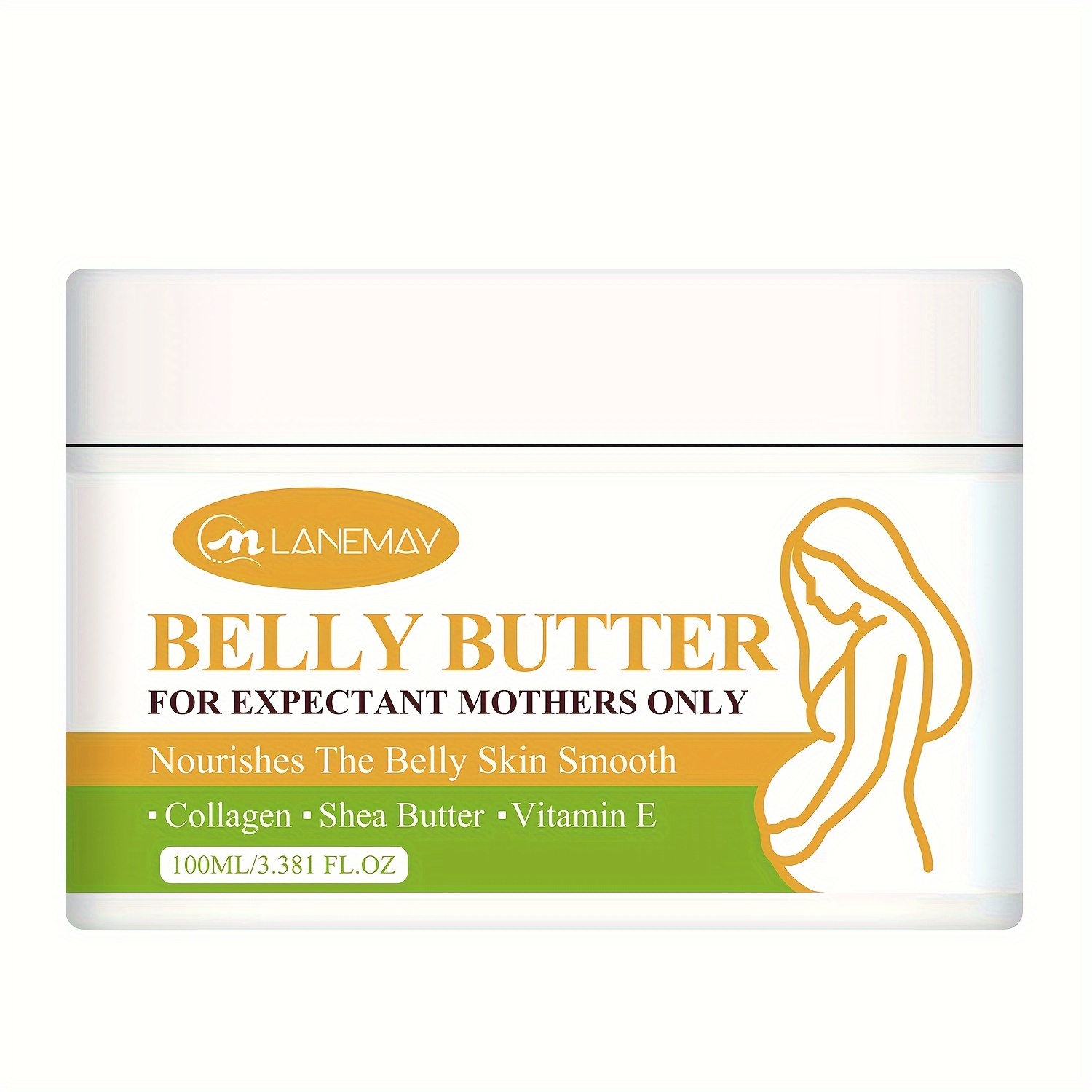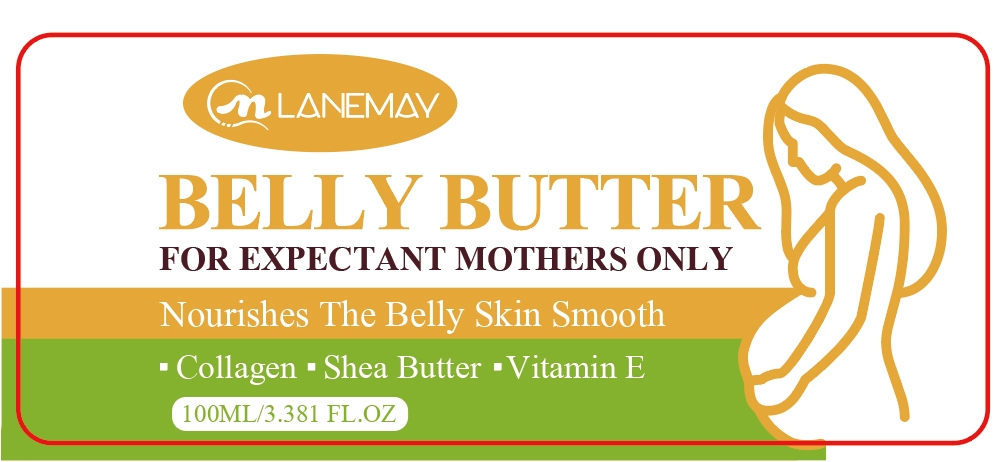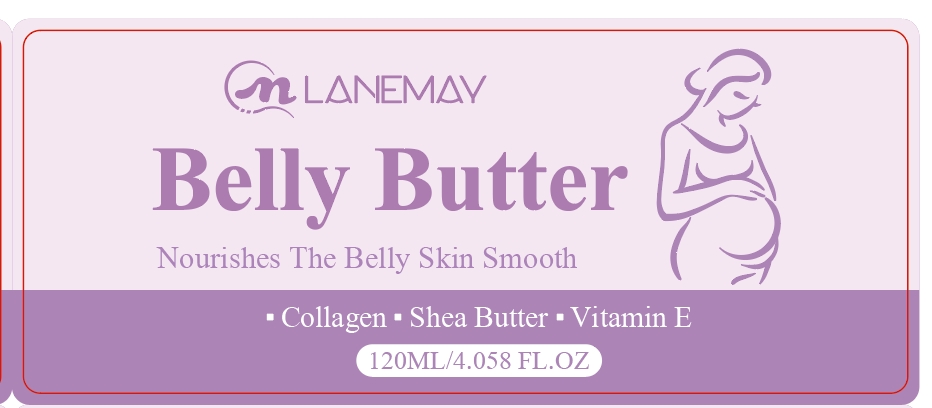 DRUG LABEL: BELLY BUTTER
NDC: 84025-052 | Form: CREAM
Manufacturer: Guangzhou Yanxi Biotechnology Co., Ltd
Category: otc | Type: HUMAN OTC DRUG LABEL
Date: 20240626

ACTIVE INGREDIENTS: MINERAL OIL 3 mg/100 mL; GLYCERIN 2 mg/100 mL
INACTIVE INGREDIENTS: WATER

DOSAGE AND ADMINISTRATION

Massage onto belly, breasts and hips every morning & night.

WARNINGS

For external use only.

INACTIVE INGREDIENT

aqua

INDICATIONS AND USAGE

Massage onto belly, breasts and hips every morning & night.

PURPOSE

Improve Skin Elasticity Texture and Tone

Keep out of reach of children.